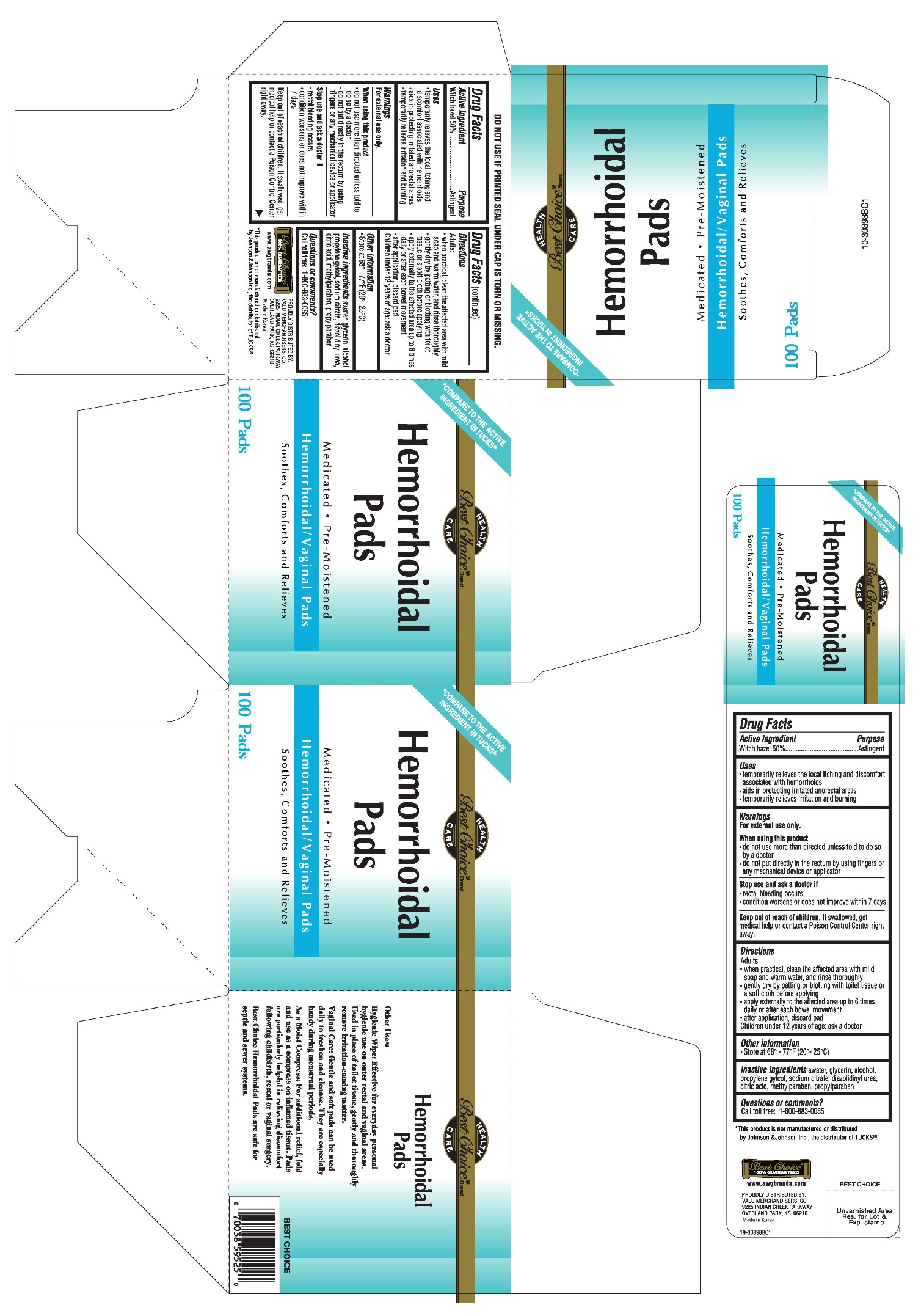 DRUG LABEL: Hemorrhoidal Pad
NDC: 63941-525 | Form: CLOTH
Manufacturer: Valu Merchandisers, Co.
Category: otc | Type: HUMAN OTC DRUG LABEL
Date: 20170426

ACTIVE INGREDIENTS: WITCH HAZEL 5 g/1 1
INACTIVE INGREDIENTS: WATER; GLYCERIN; ALCOHOL; PROPYLENE GLYCOL; SODIUM CITRATE; DIAZOLIDINYL UREA; CITRIC ACID MONOHYDRATE; METHYLPARABEN; PROPYLPARABEN

Drug Facts

Active ingredient

Witch hazel 50%

Purpose

Astringent

Uses

- temporarily relieves the local itching and discomfort associated with hemorrhoids
- aids in protecting irritated anorectal areas
- temporarily relieves irritation and burning

Warnings

For external use only.

When using this product

- do not use more than directed unless told to do so by a doctor
- do not put directly in the rectum by using fingers or any mechanical device or applicator

Stop use and ask a doctor if

- rectal bleeding occurs
- condition worsens or does not improve within 7 days

Keep out of reach of children.

If swallowed, get medical help or contact a Poison Control Center right away.

Directions

Adults:

- when practical, clean the affected area with mild soap and warm water, and rinse thoroughly
- gently dry by patting or blotting with toilet tissue or a soft cloth before applying
- apply externally to the affected area up to 6 times daily or after each bowel movement
- after application, discard pad

Children under 12 years of age: ask a doctor

Other information

- Store at 68° - 77°F (20° - 25°C)

Inactive ingredients

water, glycerin, alcohol, propylene glycol, sodium citrate, diazolidinyl urea, citric acid, methylparaben, propylparaben

Package label

Hemorrhoidal Pads